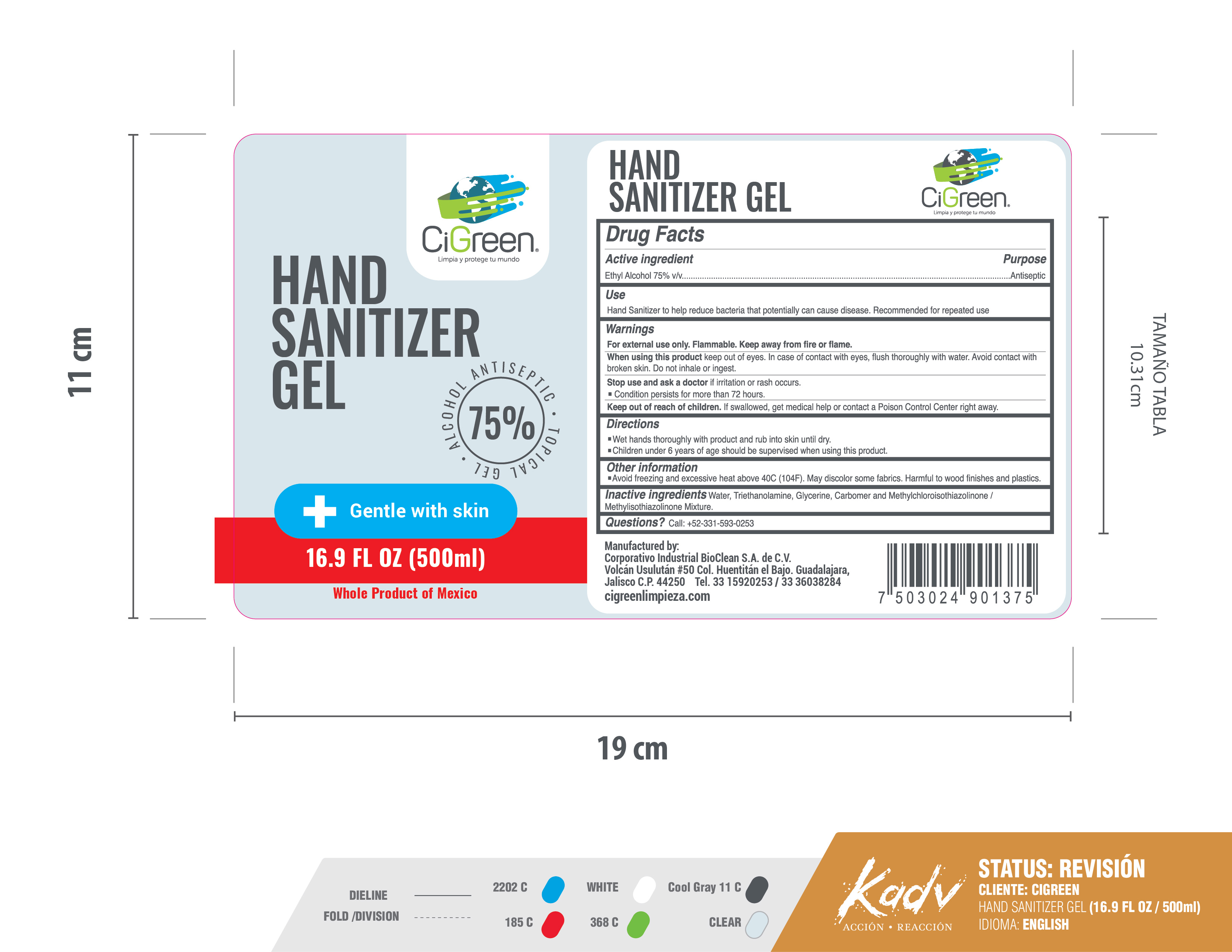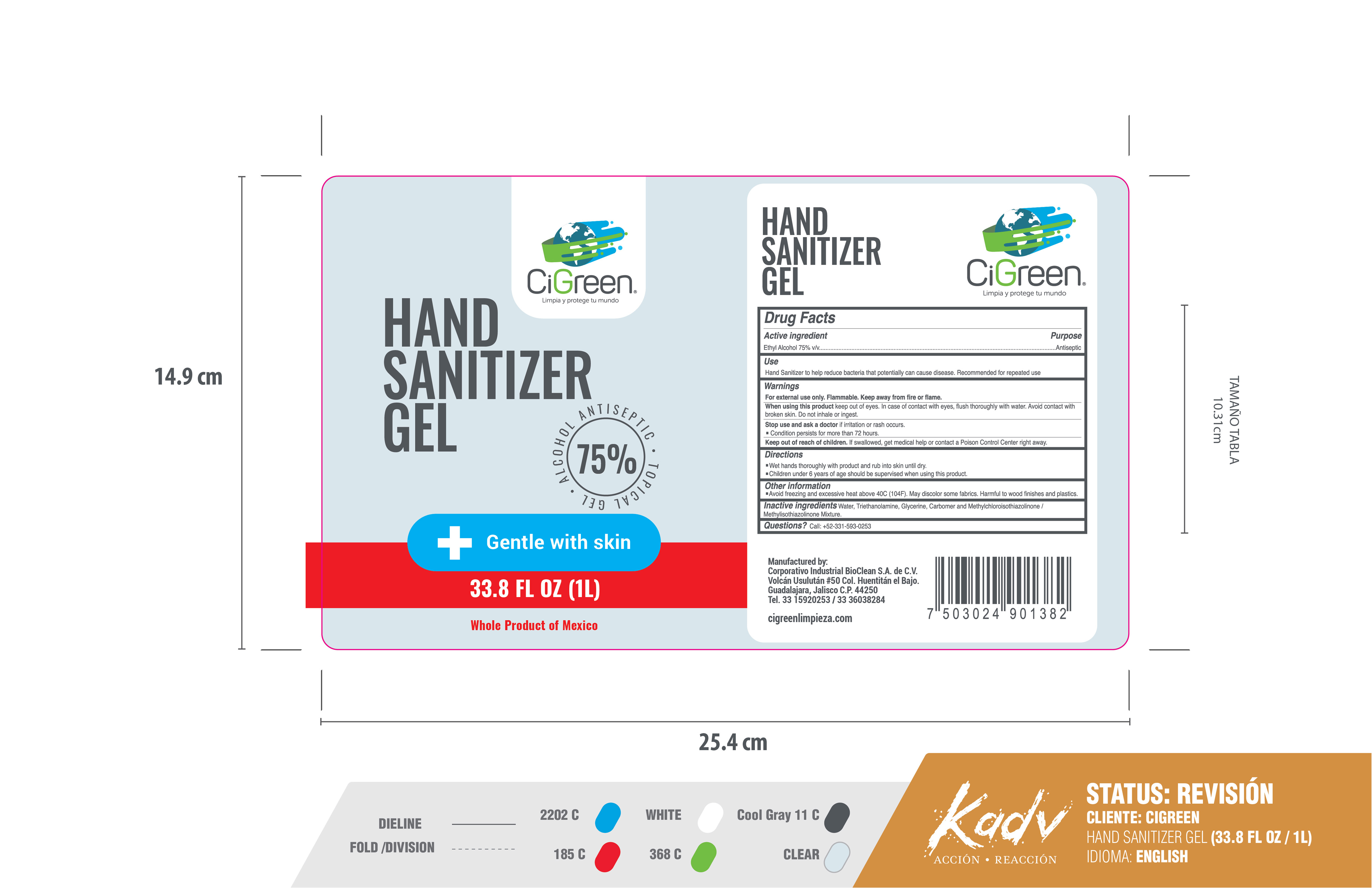 DRUG LABEL: Hand Sanitizer
NDC: 78100-100 | Form: GEL
Manufacturer: Corporativo Industrial Bioclean, S.A. de C.V.
Category: otc | Type: HUMAN OTC DRUG LABEL
Date: 20210716

ACTIVE INGREDIENTS: ALCOHOL 750 mL/1 L
INACTIVE INGREDIENTS: WATER 242.6 mL/1 L; GLYCERIN 2 mL/1 L; CARBOMER 980 3 mL/1 L; METHYLCHLOROISOTHIAZOLINONE/METHYLISOTHIAZOLINONE MIXTURE 0.4 mL/1 L; TROLAMINE 2 mL/1 L

ACTIVE INGREDIENT

Ethyl alcohol 75% v/v

PURPOSE

Antiseptic

INDICATIONS AND USAGE

Hand Sanitizer to help reduce bacteria that potentially can cause disease. Recommended for repeated use.

WARNINGS

For external use only. Flammable. Keep away from fire or flame.

When using this product keep out of eyes. In case of contact with eyes, flush thoroughly with water. Avoid contact with broken skin. Do not inhale or ingest.

Stop use and ask a doctor if irritation or rash occurs. Condition persists for more than 72 hours.

Keep out of reach of children. If swallowed, get medical help or contact a Poison Control Center right away.

DOSAGE AND ADMINISTRATION

Wet hands thoroughly with product and rub into skin until dry.

Children under 6 years of age should be supervised when using this product.

OTHER SAFETY INFORMATION

Avoid freezing and excessive heat above 40C (104F). May discolor some fabrics. Harmful to wood finishes and plastics.

INACTIVE INGREDIENT

Water, Triethanolamine, Glycerine, Carbomer and Methylchloroisothiazolinone/Methylisothiazolinone Mixture

Questions? Call +52-331-593-0253

PACKAGE LABEL

CIGREEN HAND SANITIZER GEL 1L NDC: 78100-100-10

CIGREEN HAND SANITIZER GEL 0.5 L NDC: 78100-100-20